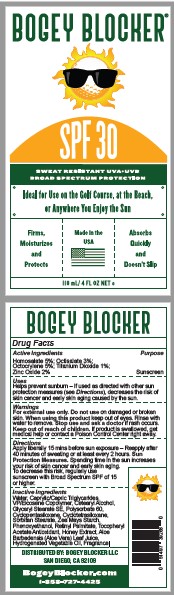 DRUG LABEL: BOGEY BLOCKER

NDC: 83386-101 | Form: LOTION
Manufacturer: Bogey Blocker LLC
Category: otc | Type: HUMAN OTC DRUG LABEL
Date: 20231003

ACTIVE INGREDIENTS: OCTISALATE 3 g/100 mL; OCTOCRYLENE 5 g/100 mL; TITANIUM DIOXIDE 1 g/100 mL; ZINC OXIDE 2 g/100 mL; HOMOSALATE 5 g/100 mL
INACTIVE INGREDIENTS: WATER; EICOSYL POVIDONE; CETOSTEARYL ALCOHOL; GLYCERYL STEARATE SE; SORBITAN MONOSTEARATE; STARCH, CORN; PHENOXYETHANOL; VITAMIN A PALMITATE; MEDIUM-CHAIN TRIGLYCERIDES; .ALPHA.-TOCOPHEROL ACETATE; POLYSORBATE 60; CYCLOMETHICONE 5; CYCLOMETHICONE 4; HONEY; ALOE VERA LEAF; HYDROGENATED PALM OIL

Bogey Blocker (as PLD) - Bogey Blocker SPF 30 (83386-101)

ACTIVE INGREDIENTS

Homosalate 5%

Octisalate 3%
Octocrylene 5%

Titanium Dioxide 1%
Zinc Oxide 2%

PURPOSE

SUNSCREEN

USES

Helps prevent sunburn – If used as directed with other sun protection measures (see Directions), decreases the risk of skin cancer and early skin aging caused by the sun.

WARNINGS

For external use only.

Do not use on damaged or broken skin.

When using this product keep out of eyes. Rinse with water to remove.

Stop use and ask a doctor if rash occurs.

Keep out of reach of children. If product is swallowed, get medical help or contact a Poison Control Center right away.

DIRECTIONS

Apply liberally 15 mins before sun exposure – Reapply after 40 minutes of sweating or at least every 2 hours. Sun Protection Measures. Spending time in the sun increases your risk of skin cancer and early skin aging. To decrease this risk, regularly use
sunscreen with Broad Spectrum SPF of 15 or higher.

INACTIVE INGREDIENTS

Water, Caprylic/Capric Triglycerides, VP/Eicosene Copolymer, Cetearyl Alcohol, Glyceryl Stearate SE, Polysorbate 60, Cyclopentasiloxane, Cyclotetrasiloxane, Sorbitan Stearate, Zea Mays Starch, Phenoxyethanol, Retinyl Palmitate, Tocopheryl
Acetate Antioxidant, Honey Extract, Aloe Barbadensis (Aloe Vera) Leaf Juice, Hydrogenated Vegetable Oil, Fragrance